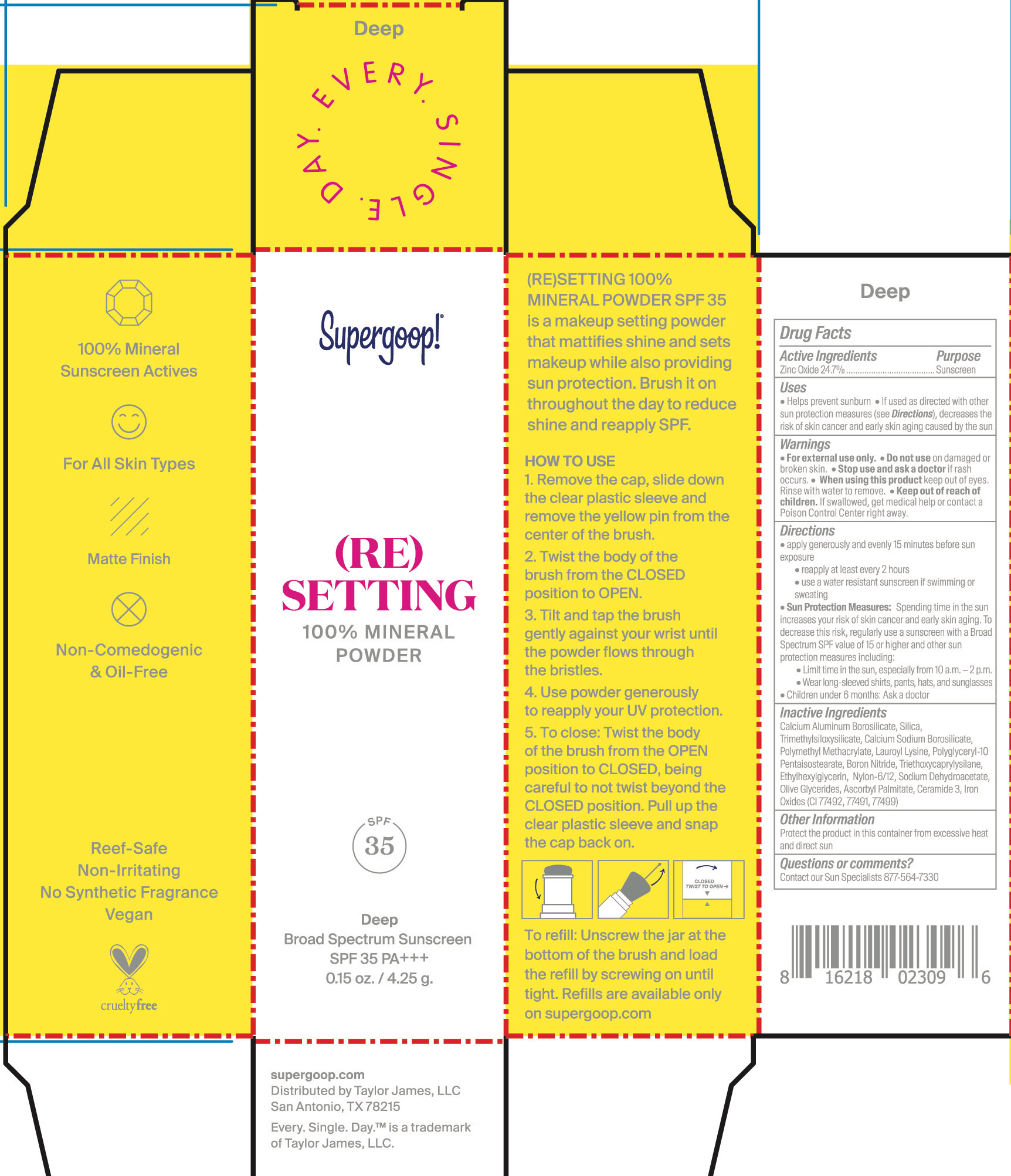 DRUG LABEL: (Re) Setting 100% mineral Powder Deep Broad Spectrum SPF 35
NDC: 75936-168 | Form: POWDER
Manufacturer: Supergoop, LLC
Category: otc | Type: HUMAN OTC DRUG LABEL
Date: 20241204

ACTIVE INGREDIENTS: ZINC OXIDE 24.7 g/100 g
INACTIVE INGREDIENTS: LAUROYL LYSINE; FERROSOFERRIC OXIDE; TRIMETHYLSILOXYSILICATE (M/Q 0.6-0.8); ASCORBYL PALMITATE; CERAMIDE 3; FERRIC OXIDE YELLOW; BORON NITRIDE; TRIETHOXYCAPRYLYLSILANE; FERRIC OXIDE RED; SILICON DIOXIDE; CALCIUM ALUMINUM BOROSILICATE; POLY(METHYL METHACRYLATE; 450000 MW); ETHYLHEXYLGLYCERIN; SODIUM DEHYDROACETATE

(Re) Setting 100% mineral Powder Deep Broad Spectrum SPF 35

Active Ingredients Purpose

Zinc Oxide 24.7% Sunscreen

Uses

- Helps prevent sunburn
- If used as directed with oher sun protection measures(see Directions), decreases the risk of skin cancer and early skin aging caused by the sun.

Keep out of reach of children. If swallowed, get medical help or contact a Poison Control Center right away.

Stop use and ask a doctor if rash occurs.

Warnings

For External use only

Do not use on damaged or broken skin

When using this product keep out of eyes. Rinse with water to remove.

Directions

- Apply generously and evenly 15 minutes before sun exposure
- Use a water-resistant sunscreen if swimming or sweating
- Reapply at least every 2 hours

- Sun Protection Measures Spending time in the sun increases your risk of

skin cancer and early skin aging. To decrease this risk, regularly use a
sunscreen with a Broad-Spectrum SPF value of 15 or higher and other sun
protection measures including: • limit your time in the sun, especially from 10
a.m. – 2 p.m. • wear long-sleeved shirts, pants, hats, and sunglasses •

- Children under 6 months of age: ask a doctor.

Inactive Ingredients

Calcium Aluminum Borosilicate, Silica, Trimethylsiloxysilicate, Calcium Sodium Borosilicate, Polymethyl Methacrylate, Lauroyl Lysine, Polyglyceryl-10 Pentaisostearate, Boron Nitride, Triethoxycaprylylsilane, Ethylhexylglycerin, Nylon-6/12, Sodium Dehydroacetate, Olive Glycerides, Ascorbyl Palmitate, Ceramide 3, Iron Oxides (CI 77492, CI 77491, CI 77499)

PACKAGE LABEL

(RE) Setting 100% Mineral Powder SPF 35 PA +++

0.12 oz/ 4.25 g